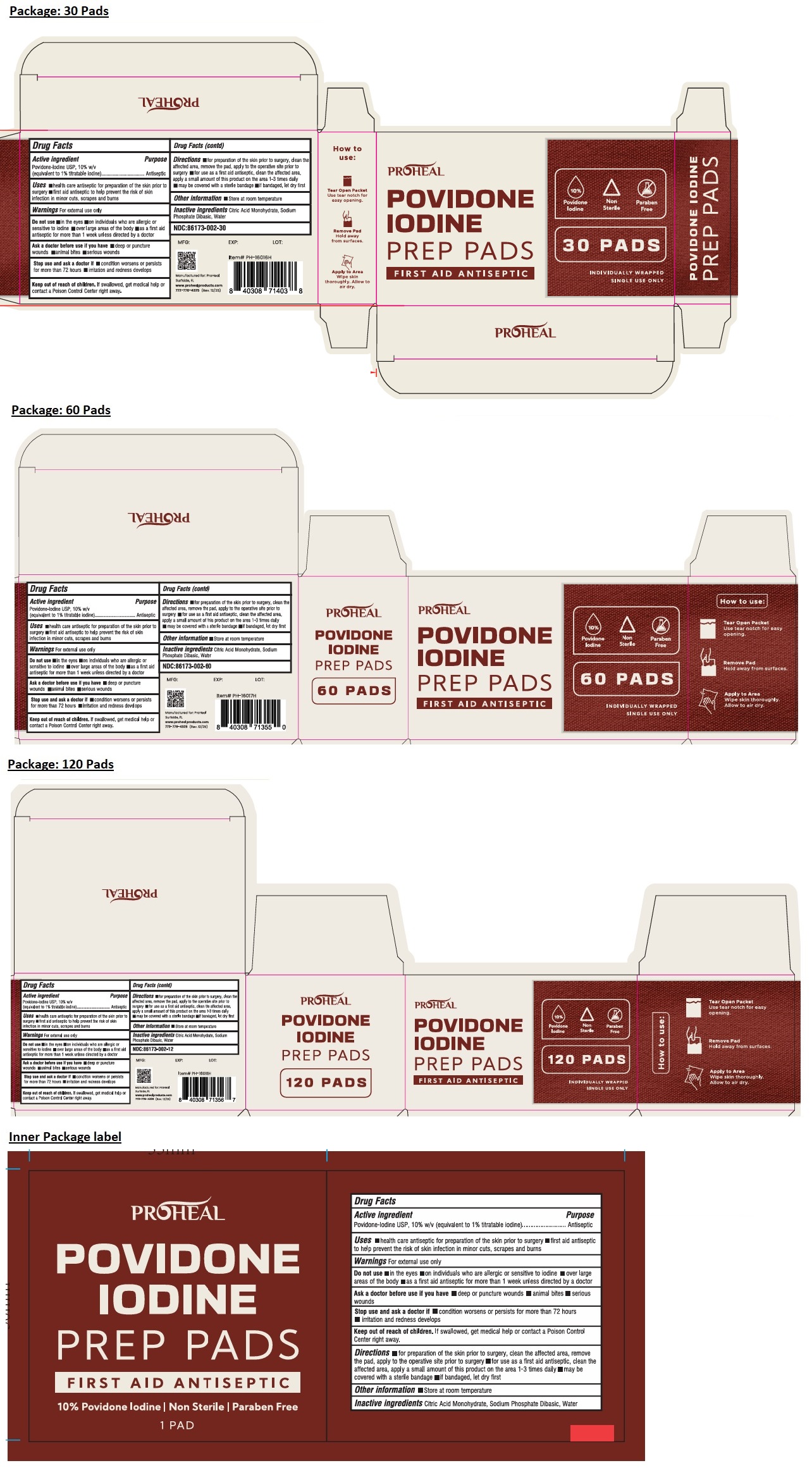 DRUG LABEL: PROHEAL POVIDONE IODINE PREP PADS
NDC: 86173-002 | Form: CLOTH
Manufacturer: Click Industries LLC
Category: otc | Type: HUMAN OTC DRUG LABEL
Date: 20251023

ACTIVE INGREDIENTS: POVIDONE-IODINE 1 g/100 mL
INACTIVE INGREDIENTS: CITRIC ACID MONOHYDRATE; SODIUM PHOSPHATE, DIBASIC, DODECAHYDRATE; WATER

PROHEAL POVIDONE IODINE PREP PADS

Active ingredient

Povidone-Iodine USP, 10% w/v (equivalent to 1% titratable iodine)

Purpose

Antiseptic

Uses

• health care antiseptic for preparation of the skin prior to surgery • first aid antiseptic to help prevent the risk of skin infection in minor cuts, scrapes and burns

Warnings

For external use only

Do not use • in the eyes • on individuals who are allergic or sensitive to iodine • over large areas of the body • as a first aid antiseptic for more than 1 week unless directed by a doctor

Ask a doctor before use if you have • deep or puncture wounds • animal bites • serious wounds

Stop use and ask a doctor if • condition worsens or persists for more than 72 hours • irritation and redness develops

Keep out of reach of children. If swallowed, get medical help or contact a Poison Control Center right away.

Directions

• for preparation of the skin prior to surgery, clean the affected area, remove the pad, apply to the operative site prior to surgery • for use as a first aid antiseptic, clean the affected area, apply a small amount of this product on the area 1-3 times daily • may be covered with a sterile bandage • if bandaged, let dry first

Other information

• Store at room temperature

Inactive ingredients

Citric Acid Monohydrate, Sodium Phosphate Dibasic, Water

FIRST AID ANTISEPTIC

Non Sterile

Paraben Free

INDIVIDUALLY WRAPPED

SINGLE USE ONLY

How to use:

Tear Open Packet
Use tear notch for easy opening.

Remove Pad
Hold away from surfaces.

Apply to Area
Wipe skin thoroughly. Allow to air dry.

Manufactured for: ProHeal Surfside, FL

www.prohealproducts.com

772-776-4325